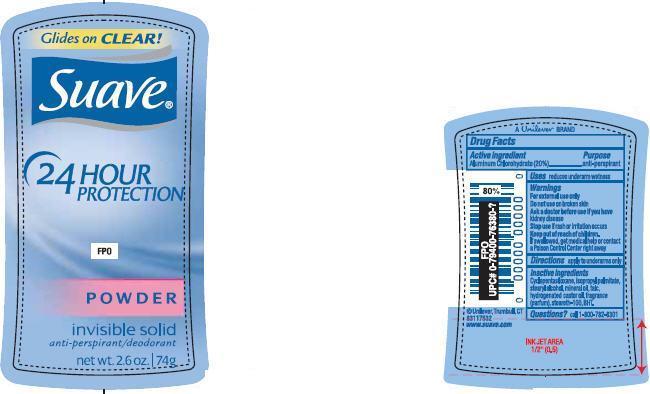 DRUG LABEL: Suave
NDC: 64942-2235 | Form: STICK
Manufacturer: Conopco Inc. d/b/a Unilever
Category: otc | Type: HUMAN OTC DRUG LABEL
Date: 20231101

ACTIVE INGREDIENTS: ALUMINUM CHLOROHYDRATE 20 g/100 g
INACTIVE INGREDIENTS: CYCLOMETHICONE 5; ISOPROPYL PALMITATE; STEARYL ALCOHOL; MINERAL OIL; TALC; HYDROGENATED CASTOR OIL; STEARETH-100; BUTYLATED HYDROXYTOLUENE

Suave 24 Hour Powder Invisible Solid Antiperspirant Deodorant

Active ingredient

Aluminum Chlorohydrate (20%)

Purpose

antiperspirant

Uses

reduces underarm wetness

Warnings

For external use only

Do not useon broken skin

Ask a doctor before use if you havekidney disease

Stop useif rash or irritation occurs

Keep out of reach of children. If swallowed, get medical help or contact a Poison Control Center right away.

Directions

apply to underarms only

Inactive Ingredients
Cyclopentasiloxane, Isopropyl Palmitate, Stearyl Alcohol, Mineral Oil, Talc, Hydrogenated Castor Oil, Fragrance (Parfum), Steareth-100, BHT.

Questions?
Call 1-800-782-8301